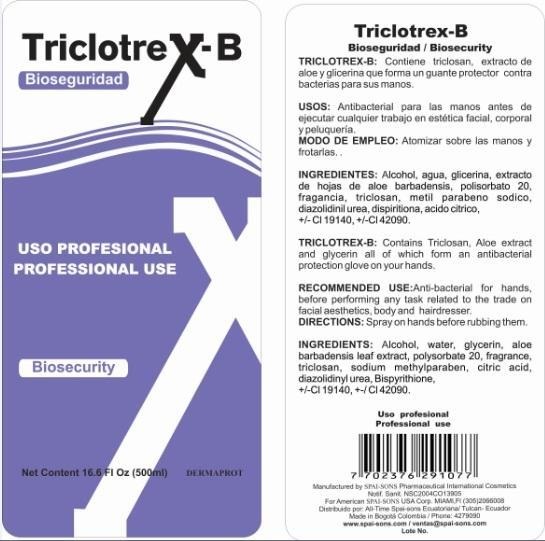 DRUG LABEL: DERMAPROT
NDC: 66854-004 | Form: LIQUID
Manufacturer: SAPI-SONS PHARMACEUTICAL INTERNATIONAL COSMETICS
Category: prescription | Type: HUMAN PRESCRIPTION DRUG LABEL
Date: 20120805

ACTIVE INGREDIENTS: TRICLOSAN 0.3 mg/100 mL
INACTIVE INGREDIENTS: ALCOHOL; WATER; GLYCERIN; ALOE VERA LEAF; POLYSORBATE 20; METHYLPARABEN SODIUM; CITRIC ACID MONOHYDRATE; DIAZOLIDINYL UREA; DIPYRITHIONE; FD&C YELLOW NO. 5; FD&C BLUE NO. 1

DERMAPROT TRICLOTREX-B

ACTIVE INGREDIENT

This product is an antibacterial liquid which produces a synergistic effect between the Triclosan is the active ingredient with a volatile carrier such as alcohol.

PURPOSE

This product is designed to produce an antibacterial effect both in the hands and utensils commonly used as combs and scissors in the facial aesthetics

KEEP OUT OF REACH OF CHILDREN

This product must be keep out of reach of children

INDICATIONS AND USAGE

This product is for topical application as well as being used in beauty salons utensils that need to be desinfected before being used.

WARNINGS

If this product to contact with eyes rinse immediately with water and consult a physician.

DOSAGE AND ADMINISTRATION

Spray an hands before rubbing them.

INACTIVE INGREDIENT

The active ingredient is in a volatile carrier of alcohol, Aloe Vera extract and glycerin to help form a protective glove on the skin and objects that are using this product.

IMAGE OF THE LABEL